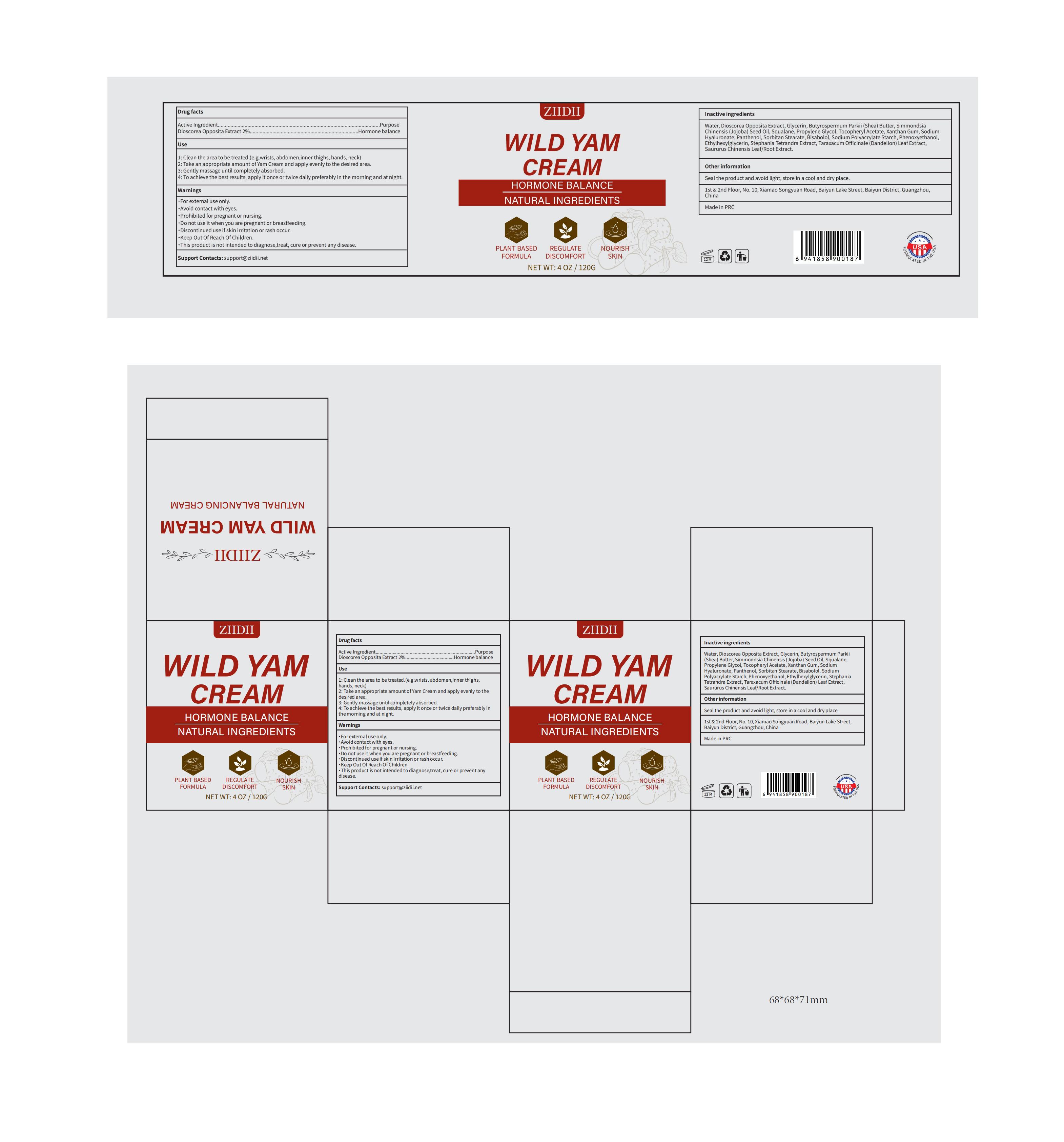 DRUG LABEL: ZIIDII Wild Yam Cream
NDC: 60771-0020 | Form: CREAM
Manufacturer: Guangzhou Haishi Biological Technology Co., Ltd.
Category: otc | Type: HUMAN OTC DRUG LABEL
Date: 20250610

ACTIVE INGREDIENTS: DIOSCOREA OPPOSITIFOLIA (WILD YAM) ROOT 2 g/100 g
INACTIVE INGREDIENTS: GLYCERIN; JOJOBA OIL; XANTHAN GUM; SQUALANE; SHEA BUTTER; OLIVE OIL

ZIIDII WILD YAM CREAM

Active ingredients

DIOSCOREA OPPOSITA EXTRACT 2%

Purpose

Hormone balance

Uses

1: Clean the area to be treated.(e.g.wrists, abdomen,innerthighs, hands, neck)
2: Take an appropriate amount of Yam Cream and apply evenly to the desired area.
3: Gently massage until completely absorbed.
4: To achieve the best results, apply it once or twice daily preferably in the morning and at night.

Warnings

For external use only.

This product is not intended to diagnose,treat, cure or prevent any disease.

Stop use and ask a doctor if

rash occurs.

Do not use

on damaged or broken skin.

Do not use it when you are pregnant or breastfeeding.

When using this product

keep out of eyes. Rinse with water to remove.

Keep out of reach of children.

If swallowed, get medical help or contact a Poison Control Center right away.

Dosage

Squeeze out an appropriate amount of product and spread evenly on skin.

Inactive ingredients

Deionized Water 76%
Glycerin 5%
Shea Butter 3%
Olive Oil 2%
Jojoba Oil 2%
Squalane 2%
Propylene Glycol 2%
Tocopheryl Acetate 1%
Xanthan Gum 0.4%
Sodium Hyaluronate 0.2%
Panthenol 1%
Sorbitan Stearate 1%
Bisabolol 0.3%
Sodium Polyacrylate Starch 0.2%
Phenoxyethanol 0.3%
Ethylhexylglycerin 0.1%
Stephania Tetrandra Extract 0.5%
Taraxacum Officinale(Dandelion) Leaf Extract 0.5%
Saururus Chinensis Leaf/Root Extract 0.5%